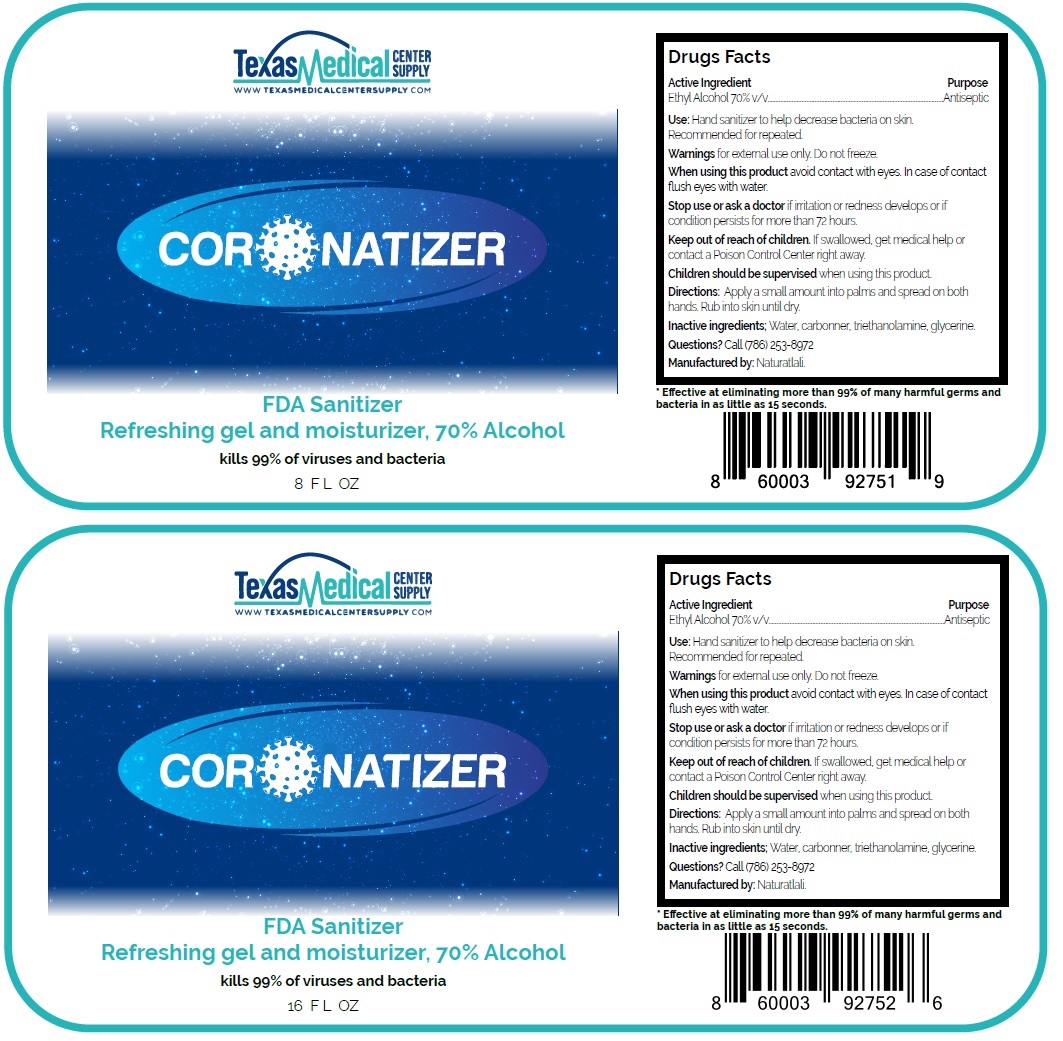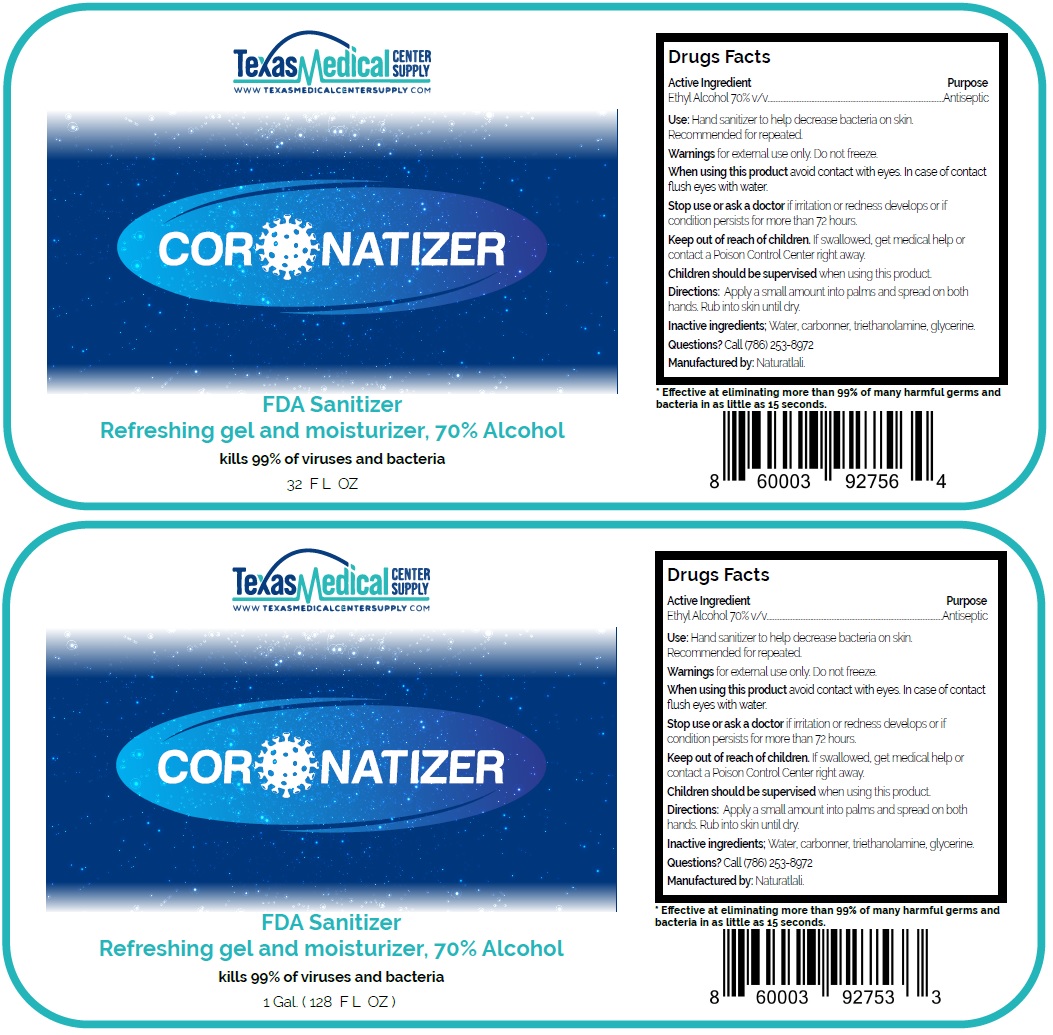 DRUG LABEL: Texas Medical Center Supply
NDC: 77788-200 | Form: GEL
Manufacturer: Texas Medical Center Supply Llc
Category: otc | Type: HUMAN OTC DRUG LABEL
Date: 20200522

ACTIVE INGREDIENTS: ALCOHOL 70 mL/100 mL
INACTIVE INGREDIENTS: WATER; CARBOMER HOMOPOLYMER, UNSPECIFIED TYPE; TROLAMINE; GLYCERIN

CORONATIZER

Active Ingredient

Ethyl Alcohol 70% v/v

Purpose

Antiseptic

INDICATIONS AND USAGE

Use: Hand sanitizer to help decrease bacteria on skin

Recommended for repeated use

Warnings for external use only. Do not freeze.

When using this product avoid contact with eyes. In case of contact flush eyes with water.

Stop use or ask a doctor if irritation or redness develops or if condition persists for more than 72 hours.

Keep out of reach of children. If swallowed, get medical help or contact a Poison Control Center right away.

Children should be supervised when using this product.

DOSAGE AND ADMINISTRATION

Directions: Apply a small amount into palms and spread on both hands. Rub into skin until dry.

Inactive ingredients; Water, carbomer, triethanolamine, glycerine.

Questions? Call (786) 253-8972

WWW.TEXASMEDICALCENTERSUPPLY.COM

FDA Sanitizer

Refreshing gel and moisturizer, 70% Alcohol

kills 99% of viruses and bacteria

Manufactured by: Naturatlali.

* Effective at eliminating more than 99% of many harmful germs and bacteria in as little as 15 seconds.